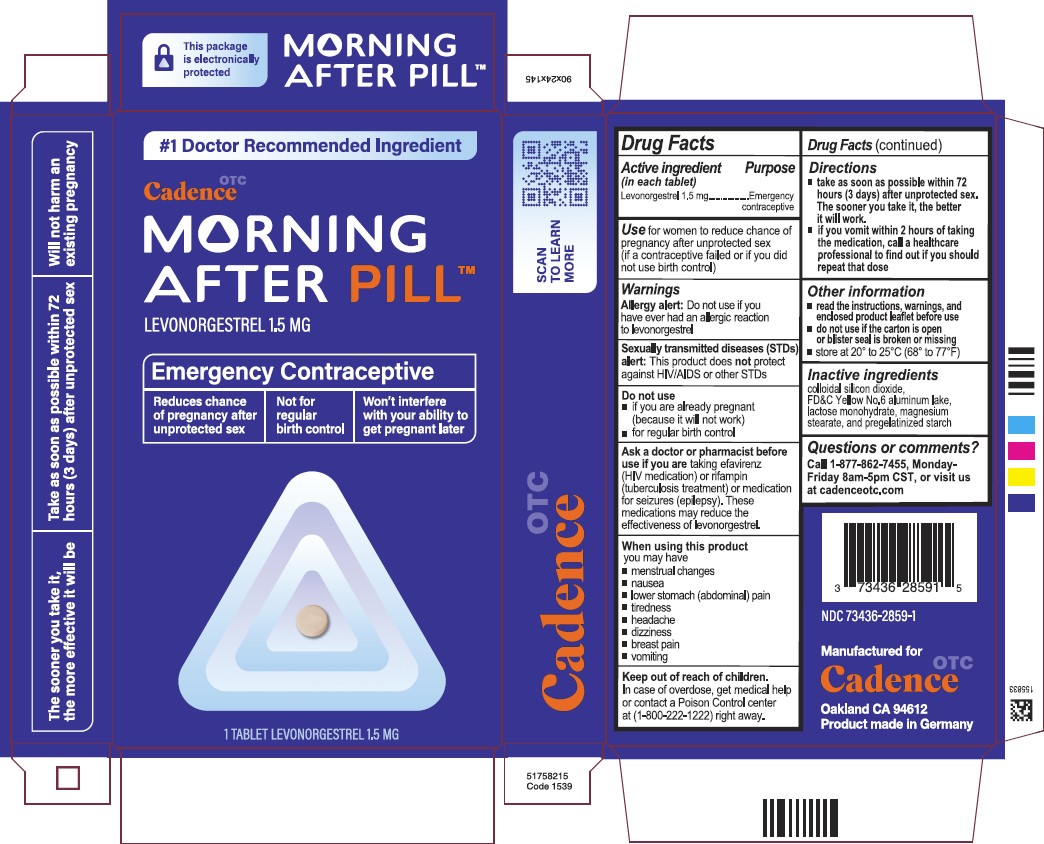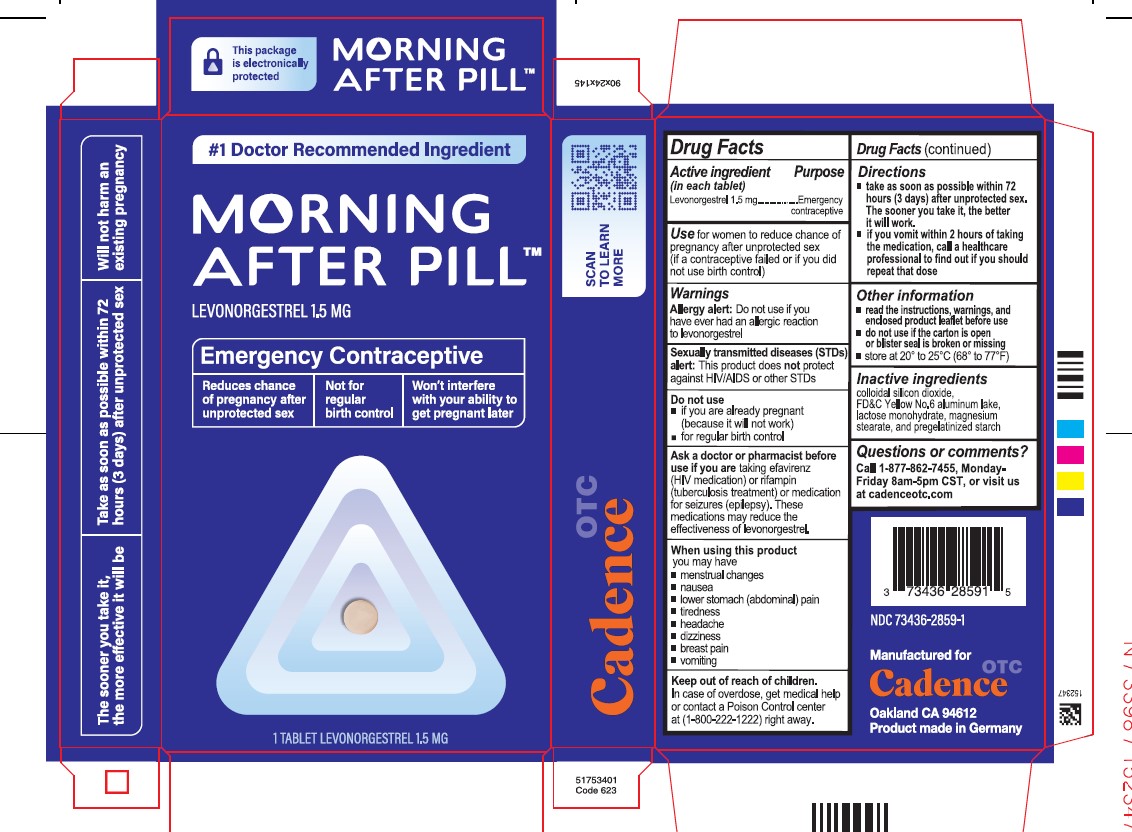 DRUG LABEL: Morning After Pill
NDC: 73436-2859 | Form: TABLET
Manufacturer: Cadence Health Inc
Category: otc | Type: HUMAN OTC DRUG LABEL
Date: 20250214

ACTIVE INGREDIENTS: LEVONORGESTREL 1.5 mg/1 1
INACTIVE INGREDIENTS: LACTOSE MONOHYDRATE; SILICON DIOXIDE; FD&C YELLOW NO. 6; STARCH, CORN; MAGNESIUM STEARATE

Active ingredient

Levonorgestrel 1.5 mg

Purpose

Emergency contraceptive

Use

for women to reduce chance of pregnancy after unprotected sex
(if a contraceptive failed or if you did not use birth control)

Allergy alert

Do not use if you have ever had an allergic reaction to levonorgestrel

Sexually transmitted diseases (STDs) alert

This product does not protect against HIV/AIDS or other STDs

Do not use

- if you are already pregnant (because it will not work)
- for regular birth control

Ask a doctor or pharmacist before use if you are taking efavirenz (HIV medication) or rifampin (tuberculosis treatment) or medication for seizures (epilepsy). These medications may reduce the effectiveness of levonorgestrel.

When using this product you may have

- menstrual changes
- nausea
- lower stomach (abdominal) pain
- tiredness
- headache
- dizziness
- breast pain
- vomiting

Keep out of reach of children. In case of overdose, get medical help or contact a Poison Control center right away 1-800-222-1222

Directions

- take as soon as possible within 72 hours (3 days) after unprotected sex. The sooner you take it, the better it will work.
- If you vomit within 2 hours of taking the medication, call a healthcare professional to find out if you should repeat the dose

Other information

- read the instructions, warnings, and enclosed product leaflet before use
- do not use if carton is open or blister seal is broken or missing
- store at 20° to 25°C (68° to 77°F)

Inactive ingredients

colloidal silicon dioxide, FD&C Yellow No.6 aluminum lake, lactose monohydrate, magnesium stearate, and pregelatinized starch

Questions or comments?

Call 1-877-862-7455
Monday - Friday 8 AM - 5 PM CST or visit us at cadenceotc.com

Manufactured for:
Cadence OTC

Oakland CA, 94612

NDC 73436-2859-1

Product made in Germany
Issued: September 2023

PACKAGE LABEL

1. NDC 73436-2859-1

Morning After PillTM

Levonorgestrel 1.5 mg

Emergency contraceptive

Reduces chance of pregnancy after unprotected sex

Not for regular birth control

Won't interefere with your ability to get pregnant later

- The sooner you take it, the more effective it will be
- Take as soon as possible within 72 hours (3 days) after unprotected sex
- Will not harm an existing pregnancy

1 TABLET LEVONORGESTREL 1.5MG